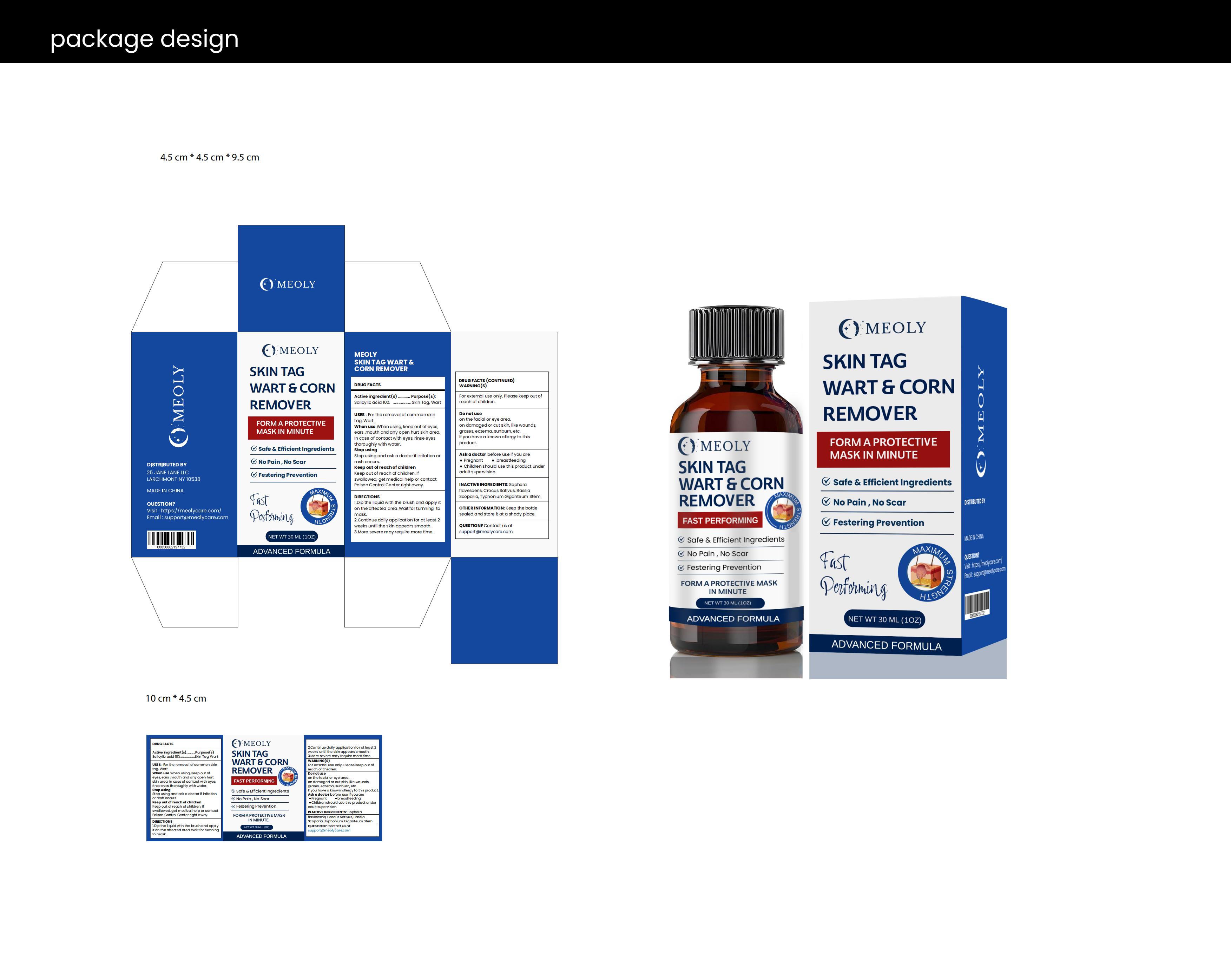 DRUG LABEL: MEOLY Skin Tag Remover
NDC: 83818-013 | Form: LIQUID
Manufacturer: Shenzhen Xinxin Yunhai Technology Co., Ltd.
Category: otc | Type: HUMAN OTC DRUG LABEL
Date: 20250603

ACTIVE INGREDIENTS: SALICYLIC ACID 10 g/100 mL
INACTIVE INGREDIENTS: SOPHORA FLAVESCENS ROOT; CROCUS SATIVUS FLOWER; SAUROMATUM GIGANTEUM ROOT; BASSIA SCOPARIA FRUIT

83818-013

Active Ingredient

Salicylic acid 10%

Purpose

Skin Tag, wart

Use

For the removal of common skintag, wart. When use When using, keep out of eyes, ears ,mouth and any open hurt skin area.
In case of contact with eyes, rinse eyes thoroughly with water.

Warnings

For external use only. Please keep out of reach of children

Do not use

on the facial or eye area. on damaged or cut skin, like wounds, grazes, eczema, sunburn, etc.
If you have a known allergy to this product.

Stop Use

Stop using and ask a doctor if irritation or rash occurs.

Ask Doctor

Ask a doctor before use if you are Pregnant breastfeeding Children should use this product under adult supervision.

Keep out of reach of children. If swallowed, get medical help or contact Poison Control Center right away

Directions

Adult s & children 4 years and over:
Wash hands before & after use. Shake well& apply 1 or 2 drops to a cotton swab and dab directly to the tags 3 times daily. Do not oversaturate or exceed dosage. It is important not to miss applications.

Children under 4 yrs: Do not use

Other information

Keep away from extreme heat. Store in a cool, dry place. Do not use if tamper-evident seal is broken or missing.

Inactive ingredients

Sophora flavescens, Crocus Sativus, Bassia Scoparia, Typhonium Giganteum Stem